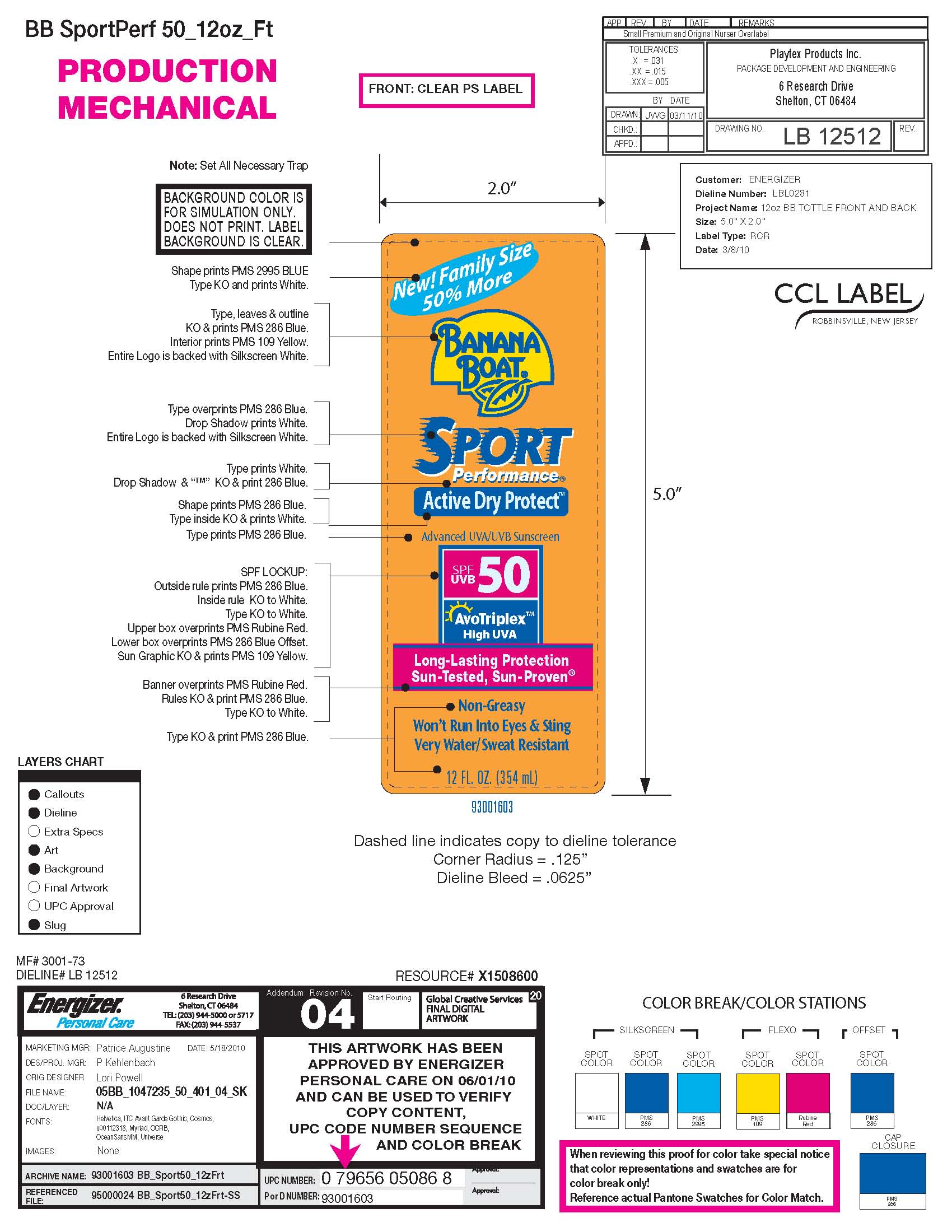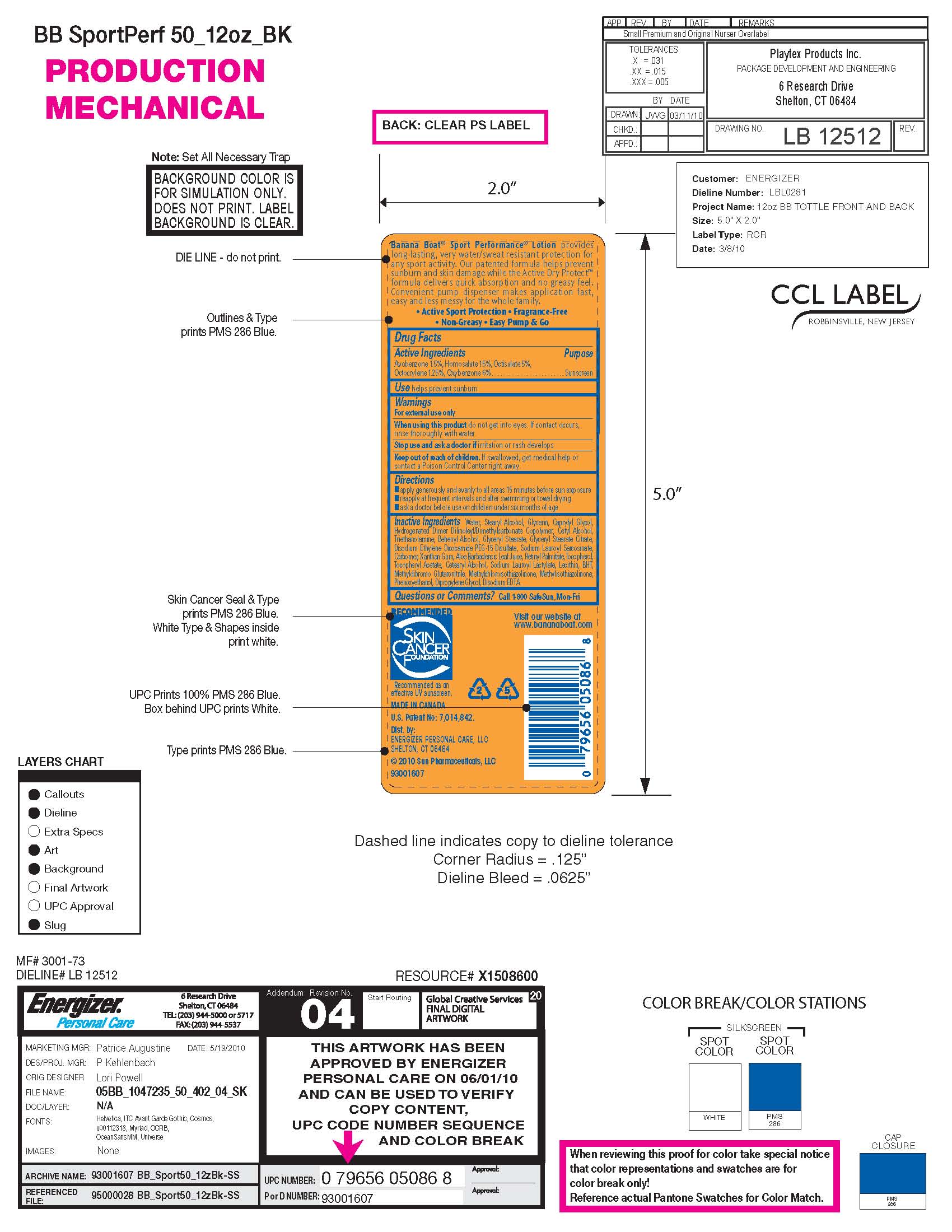 DRUG LABEL: Banana Boat Sport Performance Active Dry Protect SPF UVB 50
NDC: 61047-831 | Form: LOTION
Manufacturer: KIK Custom Products
Category: otc | Type: HUMAN OTC DRUG LABEL
Date: 20110518

ACTIVE INGREDIENTS: Homosalate 53.1 mL/354 mL; Octisalate 17.7 mL/354 mL; Octocrylene 4.42 mL/354 mL; Oxybenzone 17.7 mL/354 mL; Avobenzone 5.31 mL/354 mL
INACTIVE INGREDIENTS: Phenoxyethanol

Banana Boat Sport Performance Active Dry Protect Advanced UVA/UVB Sunscreen SPF 50 -Long Lasting Protection, Sun Tested, Sun Proven

Drug Facts:

Avobenzone:1.5%
Homosalate: 15%
Octisalate: 5%
Octocrylene: 1.25%
Oxybenzone: 5%

Purpose: Sunscreen

WARNINGS

FOR EXTERNAL USE ONLY.
WHEN USING THIS PRODUCT, DO NOT GET INTO EYES IF CONTACT OCCURS, RINSE THOROUGHLY WITH WATER.
STOP USE AND ASK DOCTOR IS IRRITATION OR RASH DEVELOPS. KEEP OUT OF REACH OF CHILDREN.
IF SWALLOWED, GET MEDICAL HELP OR CONTACT POISON CONTROL CENTER RIGHT AWAY.

INACTIVE INGREDIENT

Water, Stearyl Alcohol, Glycerin, Capryly Glycol, Hydrogenated Dimer, Dilnoleyl Dimethyl Carbonate, Copolymer,
Cetyl Alcohol, Triethanolamine, Behenyl Alcohol, Glyceryl Stearate, Glceryl Stearate Citrate, Disodium, Ethylene,
Dicocamide PEG/15 Disulfate, Sodium Lauryl Sarcosinate, Carbomer, Xanthan Gum, Aloe Barbadenis Leaf Juice, Retinyl Palmitate,
Tocophenol, Tocopheryl Acetate, Cetearyl Alcohol, Sodium Lauryl Lactylate, Leithin, BHT, Methyl Dibromo, Glutaronitrile, Methylchloroisothiazolinone,
Methylisothiazolinone, Phenoxyl Ethanol, Dipropylene Glycol, Disodium EDTA.

Questions or Comments: Call 1-800-SAFESUN Mon-Fri.

KEEP OUT OF REACH OF CHILDREN.
IF SWALLOWED, GET MEDICAL HELP OR CONTACT POISON CONTROL CENTER RIGHT AWAY.

PURPOSE

Sunscreen

Directions:

Apply generously and evenly to all areas 15 minutes before sun exposure.

Re-Apply at frequent intervals and after swimming and towel drying.
Ask a doctor for use on children under 6 months of age.